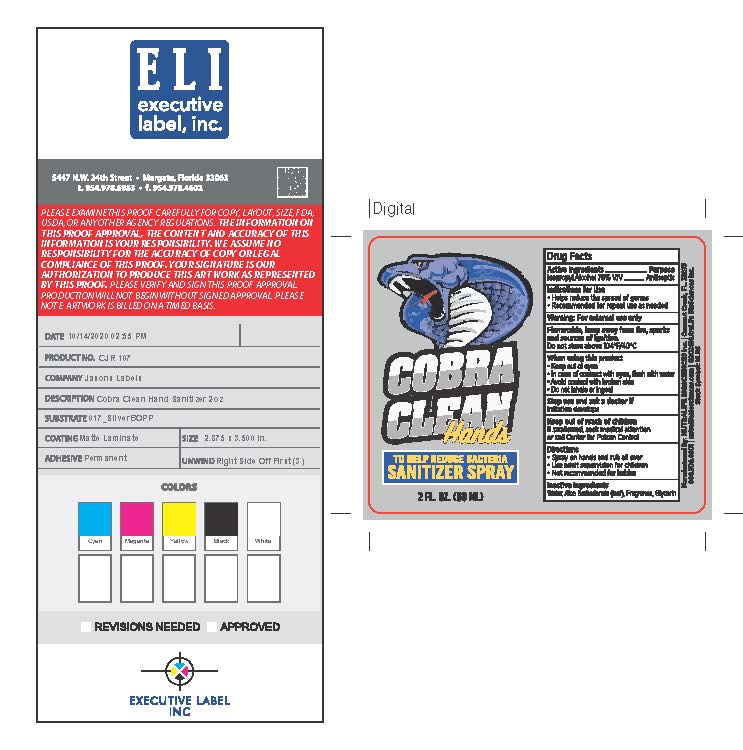 DRUG LABEL: Cobra Clean Hands
NDC: 73761-103 | Form: SPRAY
Manufacturer: Nutralife Biosciences, Inc.
Category: otc | Type: HUMAN OTC DRUG LABEL
Date: 20201020

ACTIVE INGREDIENTS: ISOPROPYL ALCOHOL 45 mL/60 mL
INACTIVE INGREDIENTS: ALOE VERA LEAF; GLYCERIN; WATER

Cobra Clean Hands

Active Ingredient

Isopropyl Alcohol 75%

Purpose

Antiseptic

Uses

Helps reduce the spread of germs
Recommended for repeat us as needed

Warnings

For External Use only
Flammable, keep away from fire, sparks, and source of ignition
Do not store above 104 F/40C

Do not Use

with any other drug containing acetaminophen (prescription or nonprescription). If you are not sure whether a drug contains acetaminophen, ask a doctor or pharmacist
if you have ever had an allergic reaction to this product or any of its ingredients

When using this product

Keep out of eyes
In case of contract with eyes, flush with water
avoid contact with broken skin
Do not inhale or ingest

Stop use and ask a doctor if

irritation develops

Keep out of reach of children

If swallowed seek medical attention or call Center for Poison Control Center

Directions

Spray on hands and rub all over
Use adult supervision for children
Not recommended for babies

Inactive Ingredients

Water, Aloe Barbadensis (leaf), Fragrance, Glycerin